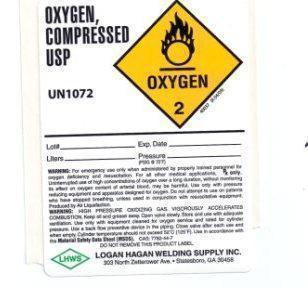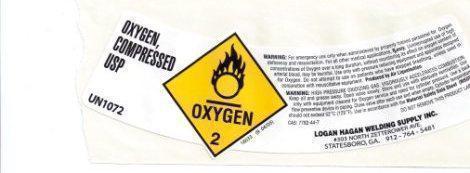 DRUG LABEL: Oxygen
NDC: 49507-001 | Form: GAS
Manufacturer: Hagan, Logan Welding Supply Inc
Category: prescription | Type: HUMAN PRESCRIPTION DRUG LABEL
Date: 20211018

ACTIVE INGREDIENTS: OXYGEN 995 mL/1 L

oxygen

PACKAGE LABEL

OXYGEN, COMPRESSED LIQUID USP UN1072 DO NOT REMOVE THIS PRODUCT LABEL.
OXYGEN 2 815033 (08/04)
WARNING: For emergency use only when administered by properly trained personnel
for oxygen deficiency and resuscitation. For all other medical applications, Rx
only.
CAUTION: Federal law prohibits dispensing without prescription. Uninterrupted
use of high concentrations of oxygen over a long duration, without monitoring
its effect on oxygen content of arterial blood, may be harmful. Use only with
pressure reducing equipment and apparatus designed for oxygen. Do not attempt to
use on patients who have stopped breathing, unless used in conjunction with
resuscitative equipment. Produced by Air Liquefaction.
WARNING: HIGH PRESSURE OXIDIZING GAS. VIGOROUSLY ACCELERATES COMBUSTION. Keep
oil, grease away. Open valve slowly. Store and use with adequate ventilation.
Use only with equipment cleaned for oxygen service and rated for cylinder
pressure. Use back flow preventive device in the piping. Close valve after each
use and when empty. Cylinder temperature should not exceed 52C (125F). Use in
accordance with the Material Safety Data Sheets (MSDS). CAS: 7782-44
-7
DO NOT REMOVE THIS PRODUCT LABEL
LOGAN HAGAN WELDING SUPPLY INC.
303 N Zetterower Ave. Statesboro, GA 30459
912-764-6481